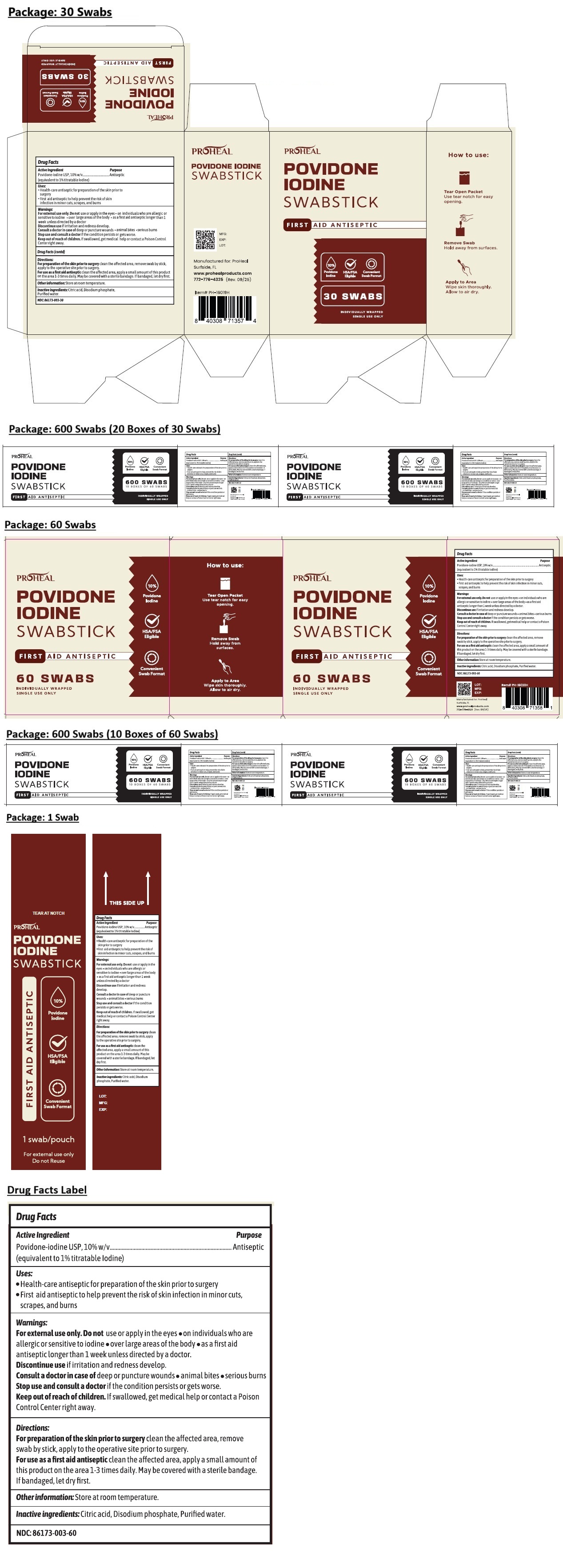 DRUG LABEL: PROHEAL POVIDONE IODINE SWABSTICK
NDC: 86173-003 | Form: SWAB
Manufacturer: Click Industries LLC
Category: otc | Type: HUMAN OTC DRUG LABEL
Date: 20251203

ACTIVE INGREDIENTS: POVIDONE-IODINE 1 g/100 mL
INACTIVE INGREDIENTS: CITRIC ACID MONOHYDRATE; SODIUM PHOSPHATE, DIBASIC, ANHYDROUS; WATER

PROHEAL POVIDONE IODINE SWABSTICK

Active Ingredient

Povidone-iodine USP, 10% w/v
(equivalent to 1% titratable Iodine)

Purpose

Antiseptic

Uses:

• Health-care antiseptic for preparation of the skin prior to surgery
• First aid antiseptic to help prevent the risk of skin infection in minor cuts, scrapes, and burns

Warnings:

For external use only. Do not use or apply in the eyes • on individuals who are allergic or sensitive to iodine • over large areas of the body • as a first aid antiseptic longer than 1 week unless directed by a doctor

Discontinue use if irritation and redness develop.

Consult a doctor in case of deep or puncture wounds • animal bites • serious burns

Stop use and consult a doctor if the condition persists or gets worse.

Keep out of reach of children. If swallowed, get medical help or contact a Poison Control Center right away.

Directions:

For preparation of the skin prior to surgery clean the affected area, remove swab by stick, apply to the operative site prior to surgery.

For use as a first aid antiseptic clean the affected area, apply a small amount of this product on the area 1-3 times daily. May be covered with a sterile bandage. If bandaged, let dry first.

Other information:

Store at room temperature.

Inactive ingredients:

Citric acid, Disodium phosphate, Purified water.

FIRST AID ANTISEPTIC

HSA/FSA Eligible

Convenient Swab Format

INDIVIDUALLY WRAPPED
SINGLE USE ONLY

How to use:

Tear Open Packet
Use tear notch for easy opening.

Remove Swab
Hold away from surfaces.

Apply to Area
Wipe skin thoroughly. Allow to air dry.

Manufactured for: ProHeal
Surfside, FL
www.prohealproducts.com